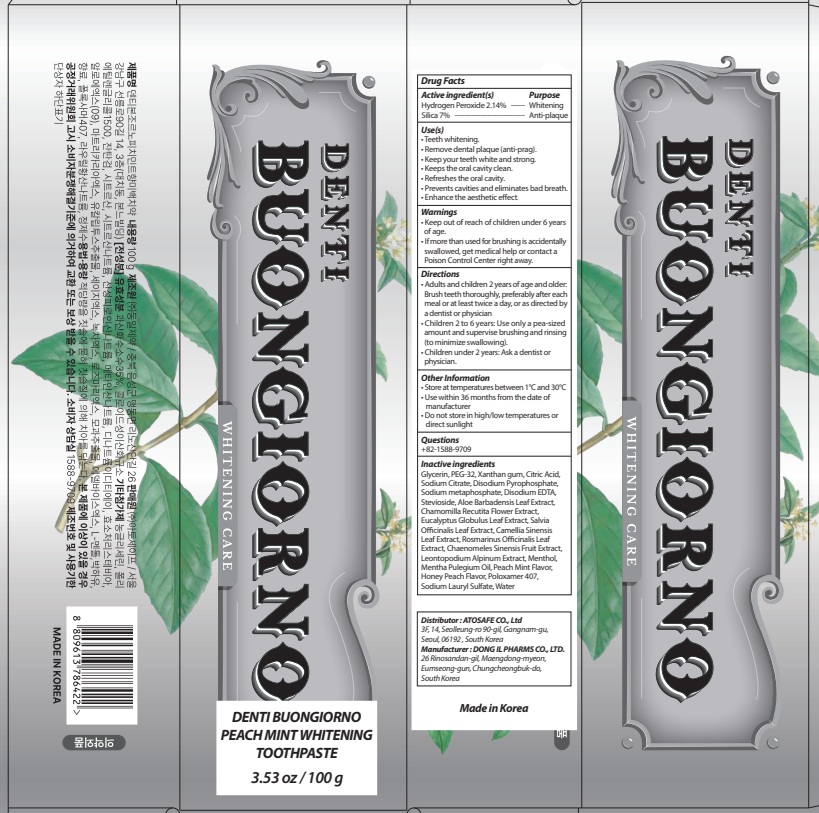 DRUG LABEL: DENTI BUONGIORNO  PEACH MINT WHITENING TOOTH
NDC: 85601-080 | Form: PASTE, DENTIFRICE
Manufacturer: ATOSAFE CO., Ltd
Category: otc | Type: HUMAN OTC DRUG LABEL
Date: 20251014

ACTIVE INGREDIENTS: SILICON DIOXIDE 7 g/100 g; HYDROGEN PEROXIDE 2.14 g/100 g
INACTIVE INGREDIENTS: XANTHAN GUM; CITRIC ACID; PEG-32; SODIUM CITRATE; GLYCERIN

Active ingredient(s)

Hydrogen Peroxide 2.14%

Silica 7%

Purpose

Whitening, Anti-plaque

Warnings

• Keep out of reach of children under 6 years of age.
• If more than used for brushing is accidentally swallowed, get medical help or contact a Poison Control Center right away.

KEEP OUT OF REACH OF CHILDREN

Keep out of reach of childrenunder 6 years of age.

INDICATIONS AND USAGE

Use(s)

• Teeth whitening.
• Remove dental plaque (anti-prag).
• Keep your teeth white and strong.

• Keeps the oral cavity clean.

• Refreshes the oral cavity.

• Prevents cavities and eliminates bad breath.

• Enhance the aesthetic effect.

Directions

• Adults and children 2 years of age and older : Brush teeth thoroughly, preferably after each meal or at least twice a day, or as directed by a dentist or physician

• Children 2 to 6 years : Use only a pea sized amount and supervise child's brushing and rinsing (to minimize swallowing)

• Children under 2 years : Ask a dentist or physician

Other Information

• Store at temperatures between 1°C and 30°C
• Use within 36 months from the date of manufacture
• Do not store in high/low temperatures or direct sunlight

Questions

+82-1588-9709

Inactive ingredients

Glycerin, PEG-32, Xanthan gum, Citric Acid, Sodium Citrate, Disodium Pyrophosphate, Sodium metaphosphate, Disodium EDTA, Stevioside, Aloe Barbadensis Leaf Extract, Chamomilla Recutita Flower Extract, Eucalyptus Globulus Leaf Extract, Salvia Officinalis Leaf Extract, Camellia Sinensis Leaf Extract, Rosmarinus Officinalis Leaf Extract, Chaenomeles Sinensis Fruit Extract, Leontopodium Alpinum Extract, Menthol, Mentha Pulegium Oil, Peach Mint Flavor, Honey Peach Flavor, Poloxamer 407, Sodium Lauryl Sulfate, Water